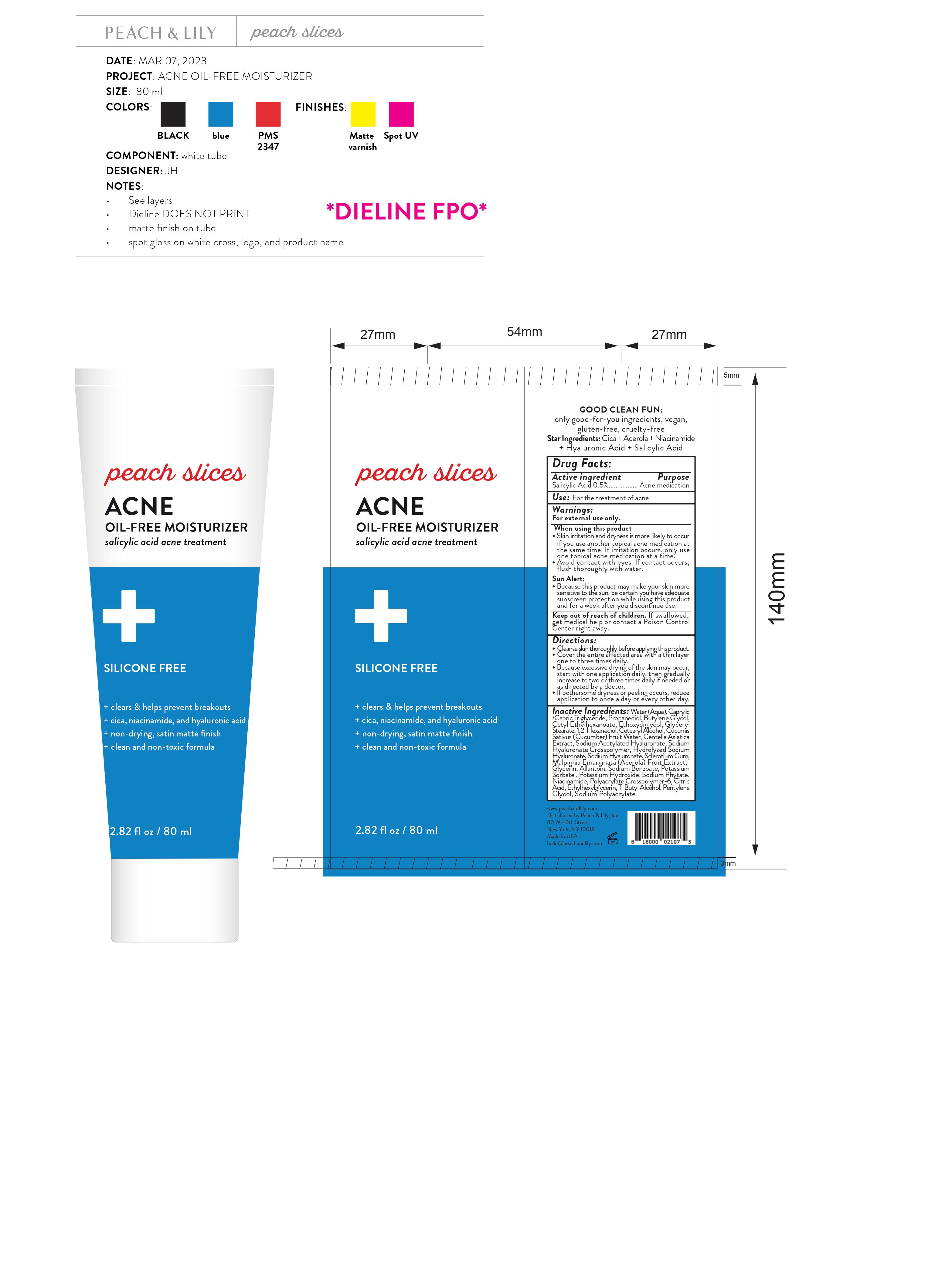 DRUG LABEL: Peach and Lily Peaches Slices Acne Oil Acne Free Moisturizer
NDC: 81515-502 | Form: GEL
Manufacturer: Peach & Lily, Inc.
Category: otc | Type: HUMAN OTC DRUG LABEL
Date: 20231028

ACTIVE INGREDIENTS: SALICYLIC ACID 5 mg/1 mL
INACTIVE INGREDIENTS: WATER; MEDIUM-CHAIN TRIGLYCERIDES; PROPANEDIOL; BUTYLENE GLYCOL; CETYL ETHYLHEXANOATE; DIETHYLENE GLYCOL MONOETHYL ETHER; GLYCERYL MONOSTEARATE; 1,2-HEXANEDIOL; CUCUMBER FRUIT OIL; SODIUM ACETYLATED HYALURONATE; HYALURONATE SODIUM; BETASIZOFIRAN; ACEROLA; GLYCERIN; ALLANTOIN; SODIUM BENZOATE; POTASSIUM SORBATE; POTASSIUM HYDROXIDE; HEXASODIUM PHYTATE; NIACINAMIDE; AMMONIUM ACRYLOYLDIMETHYLTAURATE, DIMETHYLACRYLAMIDE, LAURYL METHACRYLATE AND LAURETH-4 METHACRYLATE COPOLYMER, TRIMETHYLOLPROPANE TRIACRYLATE CROSSLINKED (45000 MPA.S); CITRIC ACID MONOHYDRATE; ETHYLHEXYLGLYCERIN; TERT-BUTYL ALCOHOL; PENTYLENE GLYCOL

Peach & Lily Peaches Slices Acne Oil Acne Free Moisturizer

Active ingredient

Salicylic Acid 0.5%

Purpose

Acne medication

Use:

For the treatment of acne

Warnings:

For external use only.

When using this product

- Skin irritation and dryness is more likely to occur if you use another topical acne medication at the same time. If irritation occurs, only use one topical acne medication at a time.
- Avoid contact with eyes. If contact occurs, flush thoroughly with water.

- Because this product may make your skin more sensitive to the sun, be certain you have adequate sunscreen protection while using this product and for a week after you discontinue use.

Sun Alert:

Keep out of reach of children.

If swallowed, get medical help or contact a Poison Control Center right away.

Directions:

- Cleanse skin thoroughly before applying this product.
- Cover the entire affected area with a thin layer one to three times daily.
- Because excessive drying of the skin may occur, start with one application daily, then gradually increase to two or three times daily if needed or as directed by a doctor.
- If bothersome dryness or peeling occurs, reduce application to once a day or every other day.

Inactive Ingredients:

Water (Aqua), Caprylic /Capric Triglyceride, Propanediol, Butylene Glycol, Cetyl Ethylhexanoate, Ethoxydiglycol, Glyceryl Stearate, 1,2-Hexanediol, Cetearyl Alcohol, Cucumis Sativus (Cucumber) Fruit Water, Centella Asiatica Extract, Sodium Acetylated Hyaluronate, Sodium Hyaluronate Crosspolymer, Hydrolyzed Sodium Hyaluronate, Sodium Hyaluronate, Sclerotium Gum, Malpighia Emarginata (Acerola) Fruit Extract, Glycerin, Allantoin, Sodium Benzoate, Potassium Sorbate , Potassium Hydroxide, Sodium Phytate, Niacinamide, Polyacrylate Crosspolymer-6, Citric Acid, Ethylhexylglycerin, T-Butyl Alcohol, Pentylene Glycol, Sodium Polyacrylate